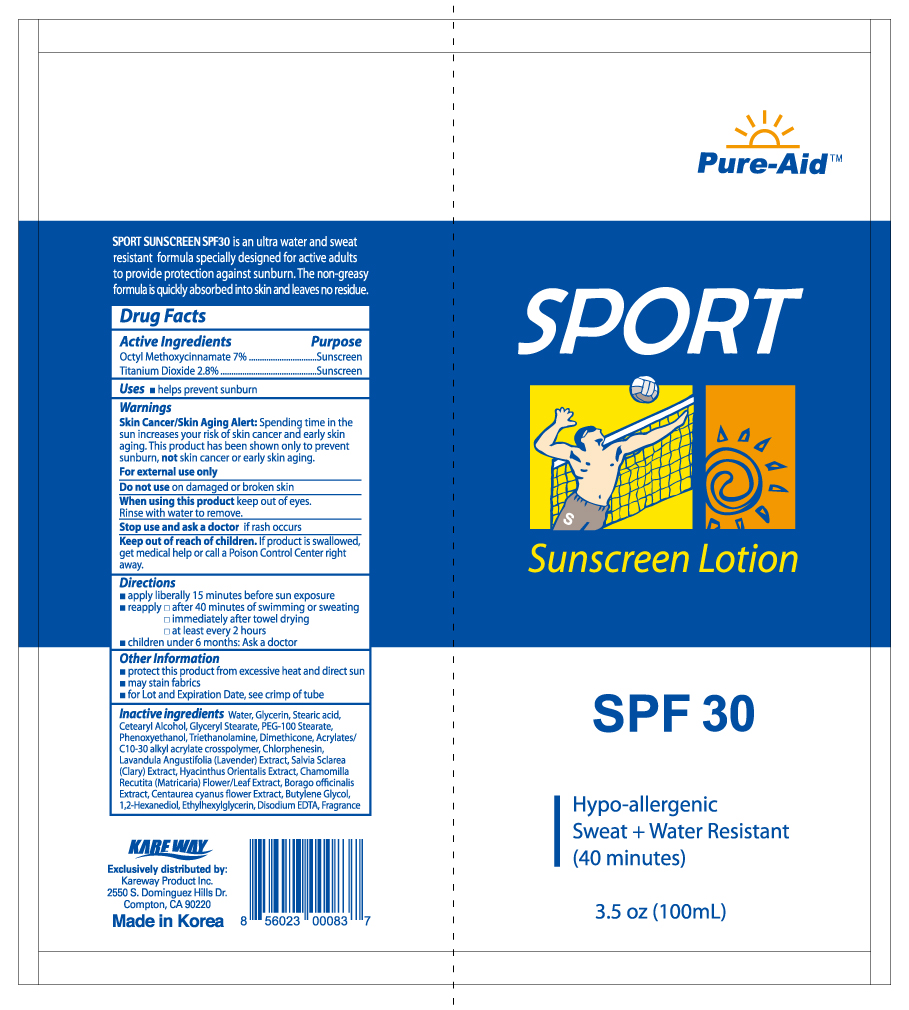 DRUG LABEL: Sport Sunblock
NDC: 67510-0083 | Form: LOTION
Manufacturer: Kareway Product, Inc.
Category: otc | Type: HUMAN OTC DRUG LABEL
Date: 20191004

ACTIVE INGREDIENTS: OCTINOXATE 7 g/100 mL; TITANIUM DIOXIDE 2.8 g/100 mL
INACTIVE INGREDIENTS: CETOSTEARYL ALCOHOL; PHENOXYETHANOL; DIMETHICONE; CARBOMER COPOLYMER TYPE A (ALLYL PENTAERYTHRITOL CROSSLINKED); GLYCERIN; GLYCERYL MONOSTEARATE; PEG-100 STEARATE; CHLORPHENESIN; BUTYLENE GLYCOL; 1,2-HEXANEDIOL; STEARIC ACID; TROLAMINE; WATER; ETHYLHEXYLGLYCERIN; EDETATE DISODIUM ANHYDROUS

Drug Facts

Active Ingredients

Octyl Methoxycinnamate 7%

Titanium Dioxide 2.8%

Purpose

Sunscreen

Sunscreen

Use

helps prevent sunburn

Warnings

Skin Cancer/Skin Aging Alert: Spending time in the sun increases your risk of skin cancer and early skin aging. This product has been shown only to prevent sunburn, not skin cancer or early skin aging.

For external use only

Do not use

on damaged or broken skin

When using this product

Keep out of eyes. Rinse with water to remove.

Stop use and ask a doctor

if rash occurs

Keep out of reach of children.

If product is swallowed, get medical help or call a Poison Control Center right away.

Directions

- apply liberally 15 minutes before sun exposure
- reapply:
-
  - after 40 minutes of swimming or sweating
  - immediately after towel drying
  - at least every 2 hours
- children under 6 months: Ask a doctor

Other information

protect this product from excessive heat and direct sun

Inactive Ingredients

Water, Glycerin, Stearic acid,

Cetearyl Alcohol, Glyceryl Stearate, PEG-100 Stearate,

Phenoxyethanol, Triethanolamine, Dimethicone, Acrylates/

C10-30 alkyl acrylate crosspolymer, Chlorphenesin,

Lavandula Angustifolia (Lavender) Extract, Salvia Sclarea

(Clary) Extract, Hyacinthus Orientalis Extract, Chamomilla

Recutita (Matricaria) Flower/Leaf Extract, Borago officinalis

Extract, Centaurea cyanus flower Extract, Butylene Glycol,

1,2- Hexanediol, Ethylhexylglycerin, Disodium EDTA, Fragrance

Package label

Sport Sunscreen